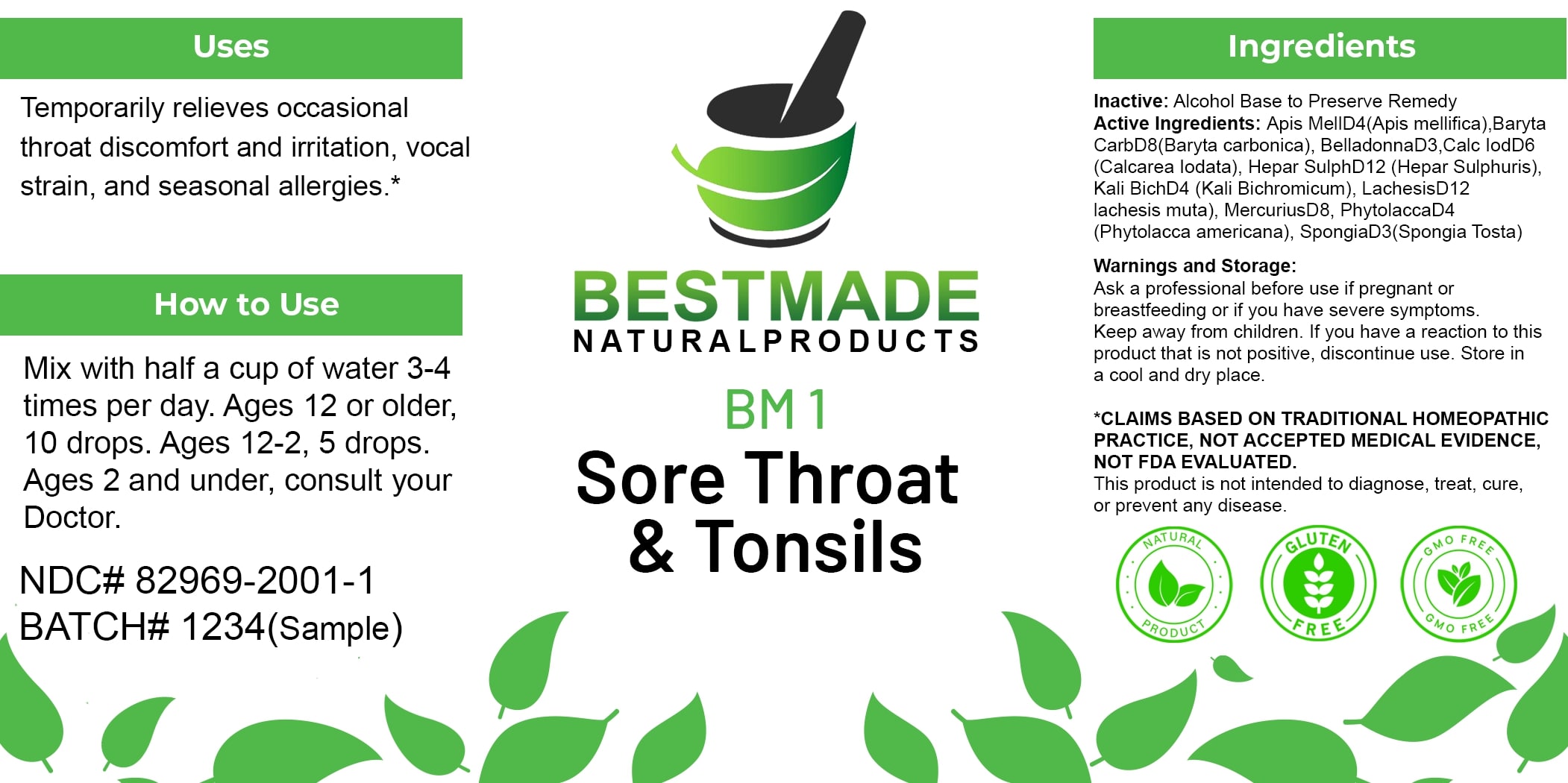 DRUG LABEL: Bestmade Natural Products BM1
NDC: 82969-2001 | Form: LIQUID
Manufacturer: Bestmade Natural Products
Category: homeopathic | Type: HUMAN OTC DRUG LABEL
Date: 20250122

ACTIVE INGREDIENTS: MERCURIUS SOLUBILIS 30 [hp_C]/30 [hp_C]; SPONGIA OFFICINALIS SKELETON, ROASTED 30 [hp_C]/30 [hp_C]; ATROPA BELLADONNA 30 [hp_C]/30 [hp_C]; POTASSIUM DICHROMATE 30 [hp_C]/30 [hp_C]; CALCIUM SULFIDE 30 [hp_C]/30 [hp_C]; PHYTOLACCA AMERICANA ROOT 30 [hp_C]/30 [hp_C]; LACHESIS MUTA VENOM 30 [hp_C]/30 [hp_C]; CALCIUM IODIDE 30 [hp_C]/30 [hp_C]; APIS MELLIFERA 30 [hp_C]/30 [hp_C]; BARIUM CARBONATE 30 [hp_C]/30 [hp_C]
INACTIVE INGREDIENTS: ALCOHOL 30 [hp_C]/30 [hp_C]

BM1

DOSAGE AND ADMINISTRATION

How to Use
Mix with half a cup of water 3-4 times per day. Ages 12 or older, 10 drops. Ages 12-2, 5 drops. Ages 2 and under, consult your Doctor.

Inactive:

Alcohol Base to Preserve Product

PURPOSE

Temporarily relieves occasional throat discomfort and irritation, vocal strain, and seasonal allergies.*

*Claims Based on Traditional Homeopathic Practice, Not Accepted Medical Evidence, Not FDA Evaluated.
This product is not intended to diagnose, treat, cure, or prevent any disease.

KEEP OUT OF REACH OF CHILDREN

Warnings and Storage:
Ask a professional before use if pregnant or breastfeeding or if you have severe symptoms. Keep away from children. If you have a reaction to this product that is not positive, discontinue use. Store in a cool and dry place.

ACTIVE INGREDIENT

Apis MellD4 (Apis mellifica), Baryta CarbD8 (Baryta carbonica), BelladonnaD3, Calc IodD6 (Calcarea Iodata), Hepar SulphD12 (Hepar Sulphuris), Kali BichD4 (Kali Bichromicum), LachesisD12 (Lachesis muta), MercuriusD8, PhytolaccaD4 (Phytolacca americana), SpongiaD3 (Spongia Tosta)

Warnings and Storage:
Ask a professional before use if pregnant or breastfeeding or if you have severe symptoms. Keep away from children. If you have a reaction to this product that is not positive, discontinue use. Store in a cool and dry place.

*Claims Based on Traditional Homeopathic Practice, Not Accepted Medical Evidence, Not FDA Evaluated.

This product is not intended to diagnose, treat, cure, or prevent any disease.

INDICATIONS AND USAGE

Temporarily relieves occasional throat discomfort and irritation, vocal strain, and seasonal allergies.*

*Claims Based on Traditional Homeopathic Practice, Not Accepted Medical Evidence, Not FDA Evaluated.
This product is not intended to diagnose, treat, cure, or prevent any disease.

Entire package label